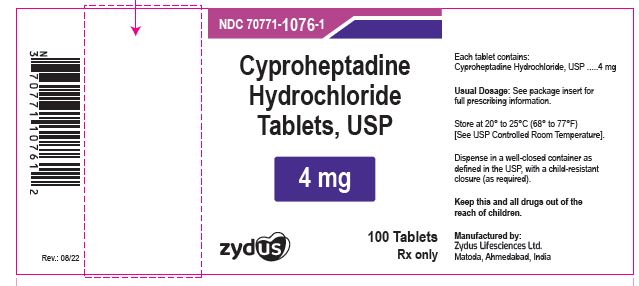 DRUG LABEL: CYPROHEPTADINE HYDROCHLORIDE
NDC: 70771-1076 | Form: TABLET
Manufacturer: Zydus Lifesciences Limited
Category: prescription | Type: HUMAN PRESCRIPTION DRUG LABEL
Date: 20241126

ACTIVE INGREDIENTS: CYPROHEPTADINE HYDROCHLORIDE 4 mg/1 1
INACTIVE INGREDIENTS: CELLULOSE, MICROCRYSTALLINE; LACTOSE MONOHYDRATE; MAGNESIUM STEARATE; SODIUM STARCH GLYCOLATE TYPE A POTATO

Cyproheptadine Hydrochloride Tablets, USP

PACKAGE LABEL.PRINCIPAL DISPLAY PANEL

NDC 70771-1076-1

Cyproheptadine Hydrochloride Tablets USP, 4 mg

100 Tablets

Rx only